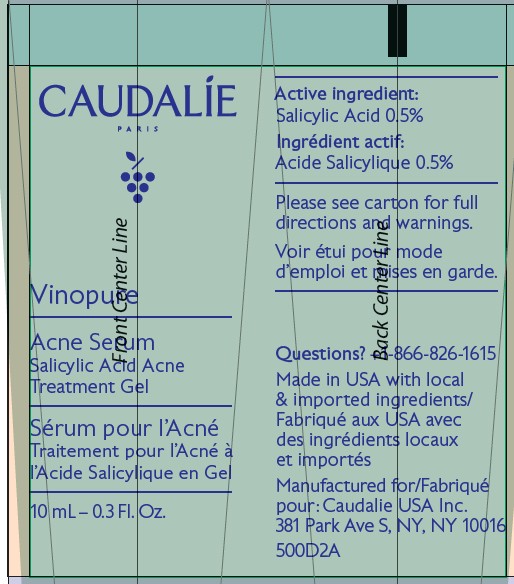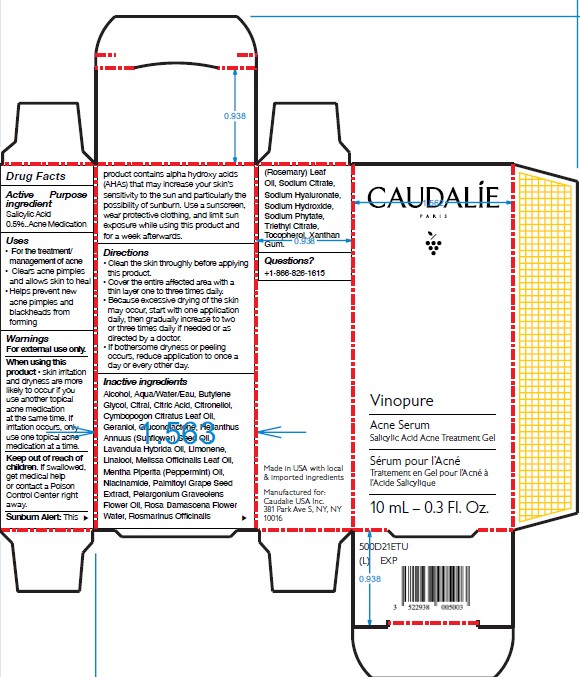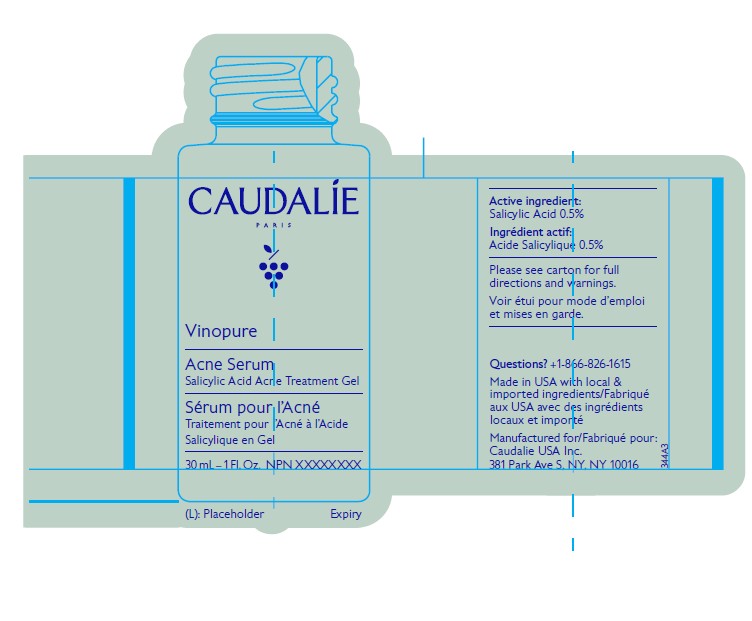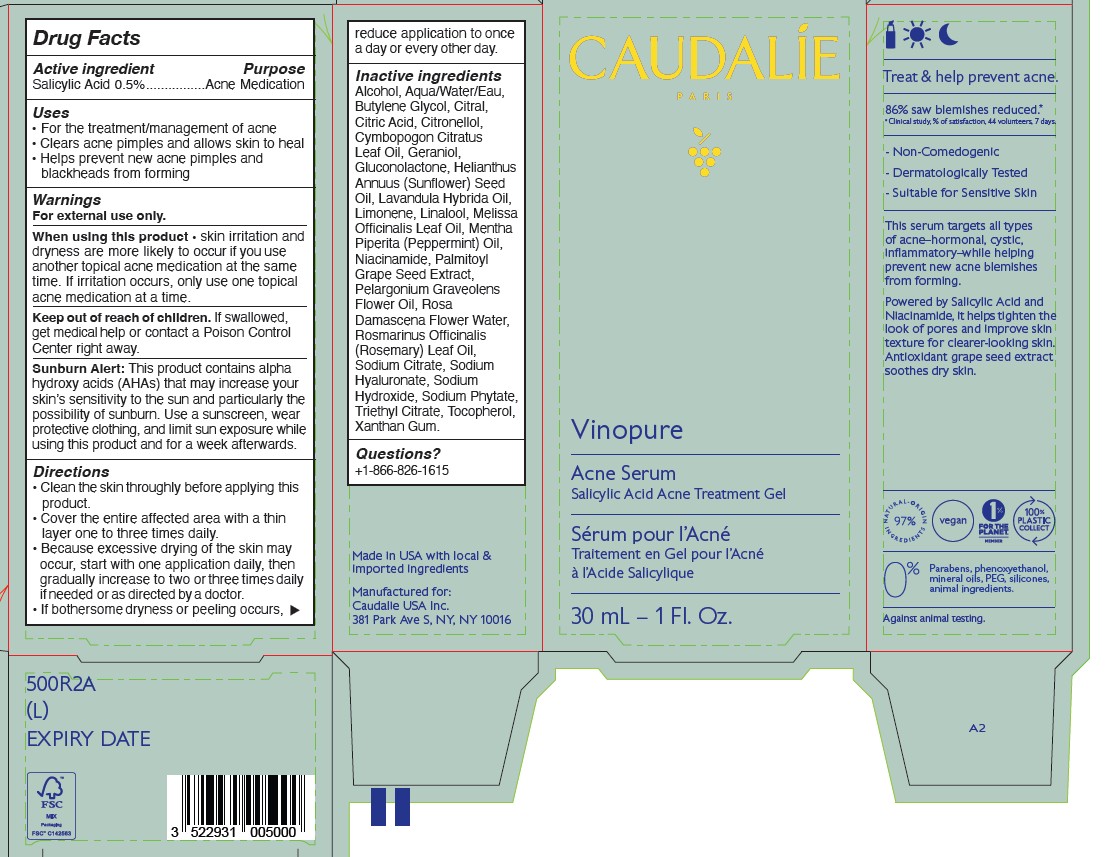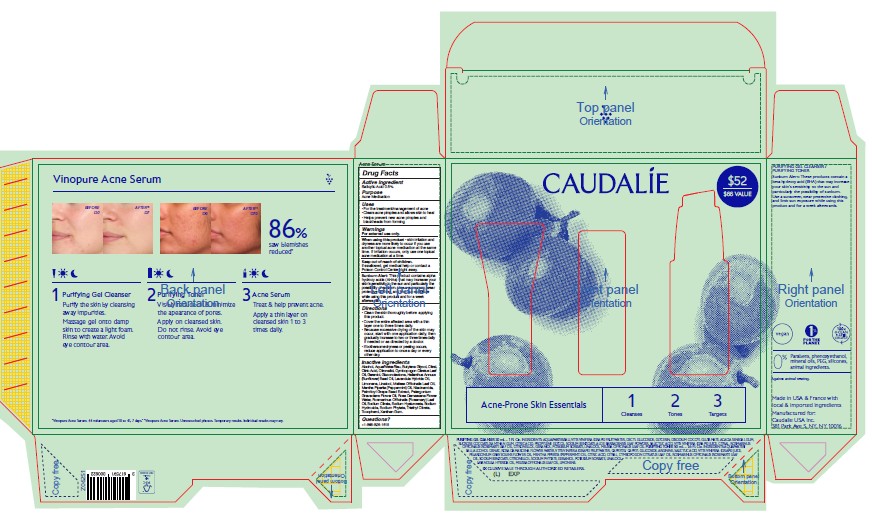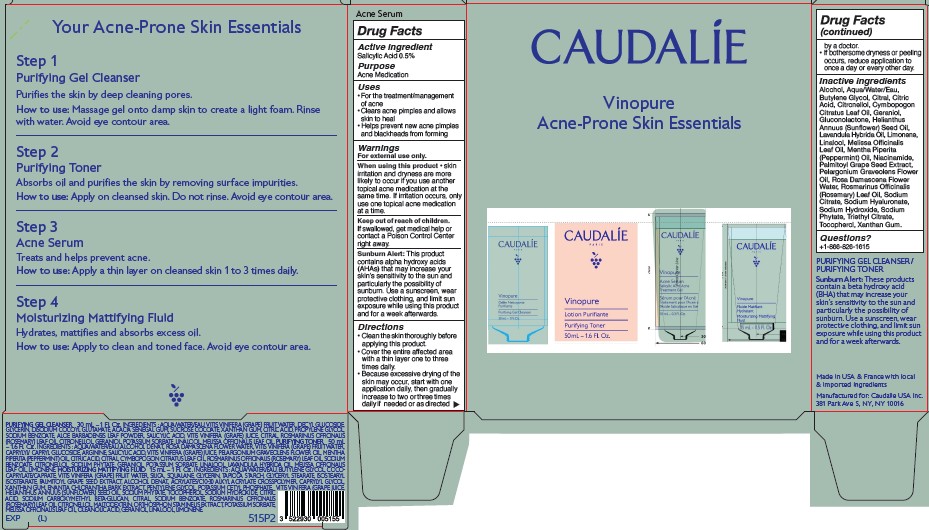 DRUG LABEL: CAUDALIE Vinopure Acne Serum
NDC: 76296-070 | Form: GEL
Manufacturer: Caudalie USA Inc.
Category: otc | Type: HUMAN OTC DRUG LABEL
Date: 20251222

ACTIVE INGREDIENTS: SALICYLIC ACID 0.15 g/30 mL
INACTIVE INGREDIENTS: ALCOHOL; BUTYLENE GLYCOL; CITRAL; CITRONELLOL; SODIUM PHYTATE; XANTHAN GUM; HELIANTHUS ANNUUS (SUNFLOWER) SEED OIL; LIMONENE, (+/-)-; PALMITOYL GRAPE SEED EXTRACT; GERANIOL; LINALOOL, (+/-)-; ROSMARINUS OFFICINALIS (ROSEMARY) LEAF OIL; MENTHA PIPERITA (PEPPERMINT) OIL; PELARGONIUM GRAVEOLENS FLOWER OIL; SODIUM HYALURONATE; SODIUM HYDROXIDE; LAVANDULA HYBRIDA OIL; MELISSA OFFICINALIS LEAF OIL; CITRIC ACID; CYMBOPOGON CITRATUS LEAF OIL; NIACINAMIDE; TRIETHYL CITRATE; .ALPHA.-TOCOPHEROL; WATER; GLUCONOLACTONE; SODIUM CITRATE; ROSA DAMASCENA FLOWER

CAUDALIE Vinopure Acne Serum
Salicylic Acid Acne Treatment Gel

Active ingredient Purpose

Salicylic Acid 0.5% ....................... Acne Medication

Active ingredient Purpose

Salicylic Acid 0.5%................Acne Medication

Uses

• For the treatment/management of acne
• Clears acne pimples and allows skin to heal
• Helps prevent new acne pimples and blackheads from forming

Warnings

For external use only.

When using this product • skin irritation and dryness are more likely to occur if you use another topical acne medication at the same
time. If irritation occurs, only use one topical acne medication at a time.

Keep out of reach of children. If swallowed, get medical help or contact a Poison Control Center right away.

WARNINGS

Sunburn Alert: This product contains alpha hydroxy acids (AHAs) that may increase your skin’s sensitivity to the sun and particularly the possibility of sunburn. Use a sunscreen, wear protective clothing, and limit sun exposure while using this product and for a week afterwards.

Directions

• Clean the skin throughly before applying this product.

• Cover the entire affected area with a thin layer one to three times daily.

• Because excessive drying of the skin may occur, start with one application daily, then gradually increase to two or three times daily if needed or as directed by a doctor.

• If bothersome dryness or peeling occurs, reduce application to once a day or every other day.

Inactive ingredients

Alcohol, Aqua/Water/Eau, Butylene Glycol, Citral, Citric Acid, Citronellol, Cymbopogon Citratus Leaf Oil, Geraniol, Gluconolactone, Helianthus Annuus (Sunflower) Seed Oil, Lavandula Hybrida Oil, Limonene, Linalool, Melissa Officinalis Leaf Oil, Mentha Piperita (Peppermint) Oil, Niacinamide, Palmitoyl Grape Seed Extract, Pelargonium Graveolens Flower Oil, Rosa Damascena Flower Water,
Rosmarinus Officinalis (Rosemary) Leaf Oil, Sodium Citrate, Sodium Hyaluronate, Sodium Hydroxide, Sodium Phytate, Triethyl Citrate, Tocopherol, Xanthan Gum.

Questions?

+1-866-826-1615

PACKAGE LABEL

CAUDALIE

Vinopure Acne Serum 30 mL - 1 Fl. Oz.

PACKAGE LABEL

CAUDALIE

Vinopure Acne Serum

10 mL - 0.3 Fl. Oz.

PACKAGE LABEL

CAUDALIE

Vinopure Acne Serum

Acne Set containing 10 mL - 0.3 Fl. Oz.

PACKAGE LABEL

CAUDALIE

Vinopure Acne Serum

Acne Set containing 30 mL - 1 Fl. Oz.